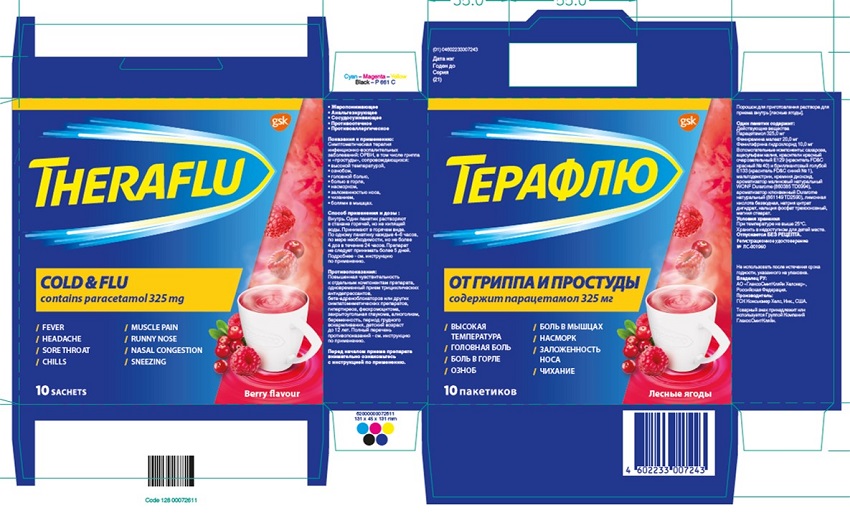 DRUG LABEL: TheraFlu Cold and Flu
NDC: 0067-0924 | Form: POWDER
Manufacturer: Haleon US Holdings LLC
Category: otc | Type: HUMAN OTC DRUG LABEL
Date: 20240502

ACTIVE INGREDIENTS: ACETAMINOPHEN 325 mg/1 1; PHENIRAMINE MALEATE 20 mg/1 1; PHENYLEPHRINE HYDROCHLORIDE 10 mg/1 1
INACTIVE INGREDIENTS: SUCROSE; ACESULFAME POTASSIUM; FD&C RED NO. 40; FD&C BLUE NO. 1; MALTODEXTRIN; SILICON DIOXIDE; ANHYDROUS CITRIC ACID; SODIUM CITRATE, UNSPECIFIED FORM; TRIBASIC CALCIUM PHOSPHATE; MAGNESIUM STEARATE

Drug Facts

TheraFlu Cold and Flu

Pharmaceutical form:Powder for oral solution (berry flavor).

Active Ingrédient

paracetamol 325.0 mg

pheniramine maleate 20.0 mg

phenylephrine hydrochloride 10.0 mg.

Purpose

- Antipyretic
- Analgesic
- Vasoconstrictive
- Decongestant
- Antiallergic

Indications:

Symptomatic therapy of infectious and inflammatory disorders: acute respiratory viral infections (ARVI) including influenza and common cold associated with: high temperature, chill, headache, sore throat, rhinitis, nasal congestion, sneezing, muscle pain.

Dosage and administration:

For oral administration. Dissolve one sachet in a glass of hot, but not boiling, water. Take hot.

Take one sachet every 4 – 6 hours as required but not more than 4 doses within 24 hours. The product should not be administered for more than 5 days.

Excipients: see patient information leaflet

Contraindications:

Hypersensitivity to individual product ingredients, co-administration of tricyclic antidepressants, beta-adrenergic blockers or other sympathomimetic products, hyperthyroidism, pheochromocytoma, angle-closure glaucoma, alcoholism, pregnancy, breastfeeding, pediatric use under 12 years of age. For a complete list of contraindications, see patient information leaflet.

Excipients:

sucrose, acesulfame potassium, Allura Red AC Е129 (FD&C red No.40), Brilliant Blue Е133 (FD&C No.1), maltodextrin, silicon dioxide, natural raspberry flavor WONF Durarome (860385 TD0994), natural cranberry Durarome flavor (861149 TD2590, citric acid anhydrous, sodium citrate dihydrate, calcium phosphate tribasic, magnesium stearate.

Storage conditions:

At temperature not higher than 25°C.

Principal Display Panel

NDC 0067-0924-01

THERAFLU

COLD & FLU

contains paracetamol 325 mg

- FEVER MUSCLE PAIN
- HEADACHE RUNNYNOSE
- SORE THROAT NASAL CONGESTION
- CHILLS SNEEZING

Berry flavour

10 SACHETS